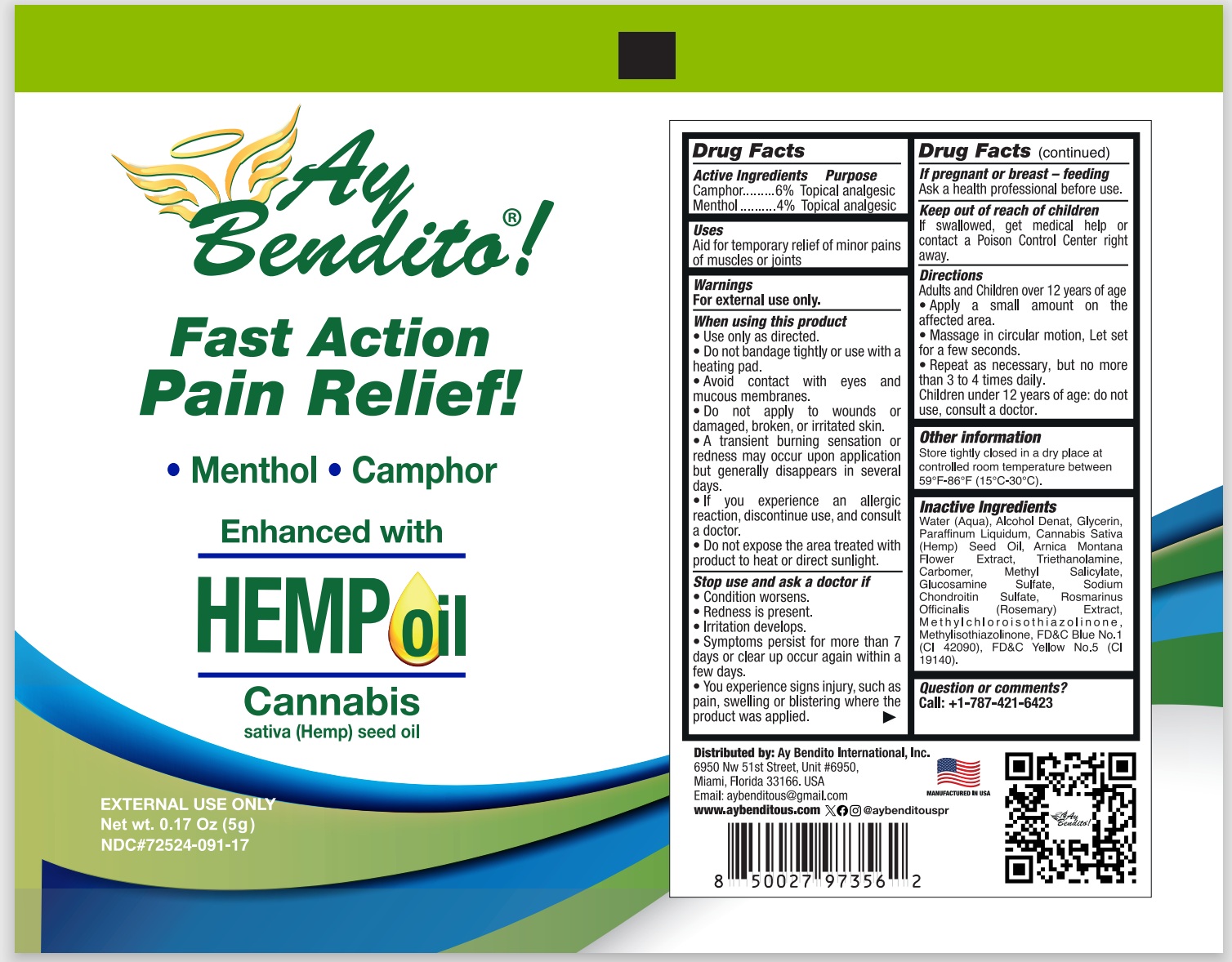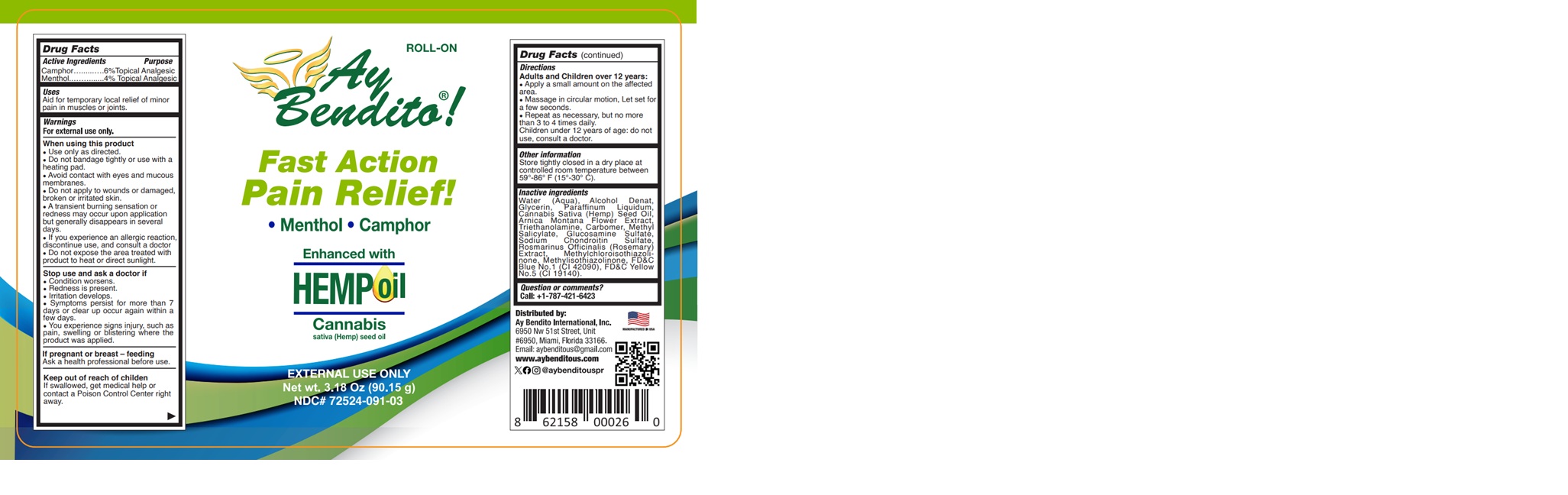 DRUG LABEL: AY BENDITO HEMP ROLL-ON
NDC: 72524-091 | Form: GEL
Manufacturer: AY BENDITO INTERNATIONAL, INC
Category: otc | Type: HUMAN OTC DRUG LABEL
Date: 20251208

ACTIVE INGREDIENTS: MENTHOL 4 g/100 g; CAMPHOR (SYNTHETIC) 6 g/100 g
INACTIVE INGREDIENTS: TROLAMINE; GLUCOSAMINE SULFATE; WATER; GLYCERIN; ARNICA MONTANA FLOWER; SODIUM CHONDROITIN SULFATE (PORCINE; 5500 MW); METHYLCHLOROISOTHIAZOLINONE; METHYLISOTHIAZOLINONE; FD&C BLUE NO. 1; METHYL SALICYLATE; ROSMARINUS OFFICINALIS WHOLE; CARBOMER HOMOPOLYMER TYPE C; MINERAL OIL; ALCOHOL; CANNABIS SATIVA SEED OIL; FD&C YELLOW NO. 5

72524-091-03
72524-091-17

Active ingredients

Camphor ………………. 6%

Menthol …………….…. 4%

PURPOSE

Topical Analgesic

Use

Aid for temporary local relief of minor pain in muscles or joints.

WARNINGS

For external use only.

When using this product

- Use only as directed
- Do not bandage tightly or use with a heating pad
- Avoid contact with eyes and mucous membranes
- Do not apply to wounds or damaged, broken or irritated skin
- A transient burning sensation or redness may occur upon application but generally disappears in several days
- If you experience an allergic reaction, discontinue use and consult a doctor
- Do not expose the area treated with product to heat or direct sunlight.

Stop use and ask a doctor if

Condition worsens
Redness is present
Irritation develops
Symptoms persist for more than 7 days or clear up occur again within a few days

You experience signs injury, such as pain, swelling or blistering where the product was applied.

If pregnant of breast feeding

Ask a health professional before use.

KEEP OUT OF REACH OF CHILDREN

If swallowed, get medical help or contact a Poison Control Center right away.

Directions

Adults and Children over 12 years of age:

Apply a small amount on the affected area.
Massage in circular motion, let set for a few seconds.
Repeat as necessary, but no more than 3 to 4 times daily.
Children under 12 years of age: do not use, consult a doctor.

Other information

Store tightly closed in a dry place at controlled room temperature between 59°- 86° F (15°- 30° C).

INACTIVE INGREDIENT

Water (Aqua), Alcohol Denat, Glycerin, Paraffinum Liquidum, Cannabis Sativa (Hemp) Seed Oil, Arnica Montana Flower Extract, Triethanolamine, Carbomer, Methyl Salicylate, Glucosamine Sulfate, Sodium Chondroitin Sulfate, Rosmarinus Officinalis (Rosemary) Extract, Methylchloroisothiazolinone, Methylisothiazolinone, FD&C Blue No.1 (CI 42090), FD&C Yellow No. 5.

QUESTION OR COMMENTS?

Call: +1-787-421-6423